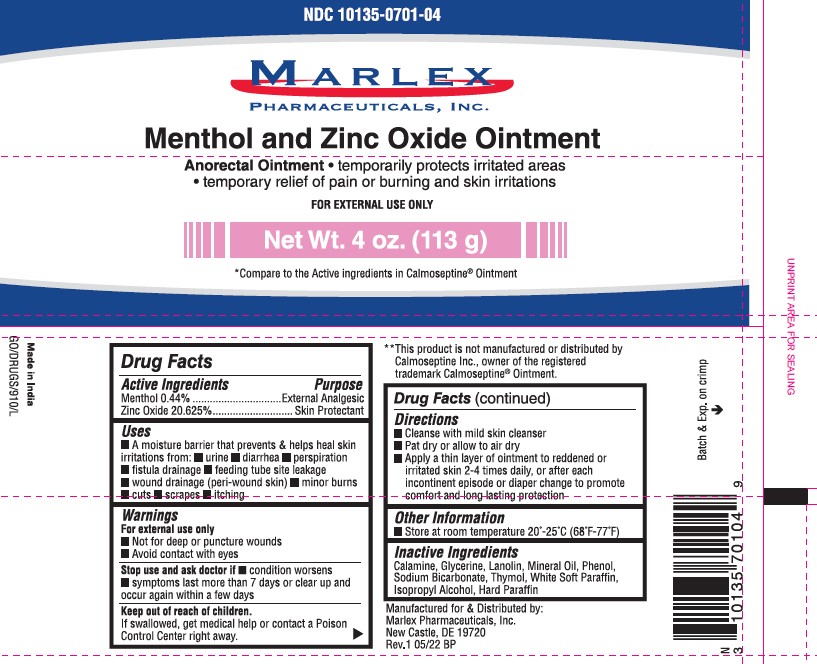 DRUG LABEL: Menthol and Zinc Oxide
NDC: 10135-701 | Form: OINTMENT
Manufacturer: Marlex Pharmaceuticals, Inc.
Category: otc | Type: HUMAN OTC DRUG LABEL
Date: 20251204

ACTIVE INGREDIENTS: MENTHOL 0.44 g/100 g; ZINC OXIDE 20.625 g/100 g
INACTIVE INGREDIENTS: GLYCERIN; SODIUM BICARBONATE; WHITE PETROLATUM; LANOLIN; THYMOL; FERRIC OXIDE RED; MINERAL OIL; PARAFFIN; PHENOL; ISOPROPYL ALCOHOL

Menthol and Zinc Oxide Ointment – anorectal Ointment

Active Ingredients

Menthol 0.44%

Zinc Oxide 20.625%

Purpose

External Analgesic

Skin Protectant

Uses

A moisture barrier that prevents & helps heal skin irritations from:

- Urine
- Diarrhea
- Perspiration
- Fistula drainage
- Feeding tube site leakage
- Wound drainage (peri-wound skin)
- Minor burns
- Cuts
- Scrapes
- Itching

Warnings

For external use only

- Not for deep or puncture wounds
- Avoid contact with eyes

Stop use and ask doctor if

- Condition worsens
- Symptoms last more than 7 days or clear up and occur again within a few days.

Keep out of reach of children

If swallowed, get medical help or contact a Poison Control Center right away.

Directions

- Cleans with mild skin cleanser
- Pat dry or allow to air dry
- Apply a thin layer of ointment to reddened or irritated skin 2-4 times daily, or after each incontinent episode or diaper change to promote comfort and long lasting protection.

Other Information

- Store at room temperature 20°- 25° C (68°F-77°F)

Inactive Ingredients

Calamine, Glycerine, Lanolin, Mineral Oil, Phenol, Sodium Bicarbonate, Thymol, White Soft Paraffin, Isopropyl Alcohol, Hard Paraffin

Package label

Menthol and Zinc Oxide Ointment